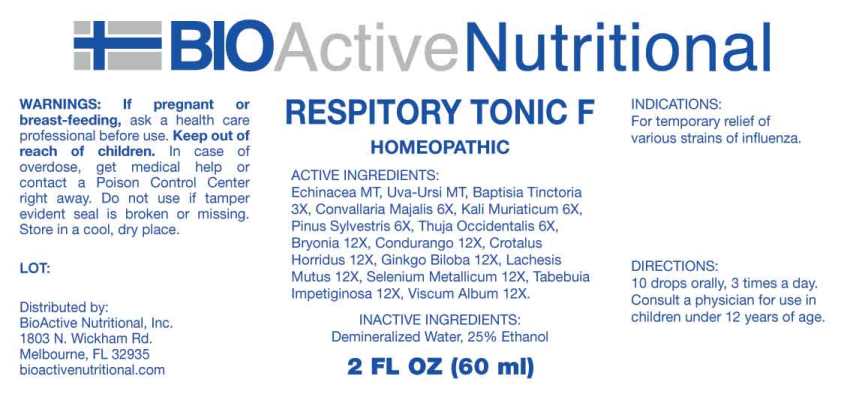 DRUG LABEL: Respitory Tonic F
NDC: 43857-0583 | Form: LIQUID
Manufacturer: BioActive Nutritional, Inc.
Category: homeopathic | Type: HUMAN OTC DRUG LABEL
Date: 20240912

ACTIVE INGREDIENTS: ECHINACEA ANGUSTIFOLIA WHOLE 1 [hp_X]/1 mL; ARCTOSTAPHYLOS UVA-URSI LEAF 1 [hp_X]/1 mL; BAPTISIA TINCTORIA ROOT 3 [hp_X]/1 mL; CONVALLARIA MAJALIS 6 [hp_X]/1 mL; POTASSIUM CHLORIDE 6 [hp_X]/1 mL; PINUS SYLVESTRIS LEAFY TWIG 6 [hp_X]/1 mL; THUJA OCCIDENTALIS LEAFY TWIG 6 [hp_X]/1 mL; BRYONIA ALBA ROOT 12 [hp_X]/1 mL; MARSDENIA CONDURANGO BARK 12 [hp_X]/1 mL; CROTALUS HORRIDUS HORRIDUS VENOM 12 [hp_X]/1 mL; GINKGO 12 [hp_X]/1 mL; LACHESIS MUTA VENOM 12 [hp_X]/1 mL; SELENIUM 12 [hp_X]/1 mL; TABEBUIA IMPETIGINOSA BARK 12 [hp_X]/1 mL; VISCUM ALBUM FRUITING TOP 12 [hp_X]/1 mL
INACTIVE INGREDIENTS: WATER; ALCOHOL

DRUG FACTS:

ACTIVE INGREDIENTS:

Echinacea (Angustifolia) 1X, Uva-Ursi 1X, Baptisia Tinctoria 3X, Convallaria Majalis 6X, Kali Muriaticum 6X, Pinus Sylvestris 6X, Thuja Occidentalis 6X, Bryonia (Alba) 12X, Condurango 12X, Crotalus Horridus 12X, Ginkgo Biloba 12X, Lachesis Mutus 12X, Selenium Metallicum 12X, Tabebuia Impetiginosa 12X, Viscum Album 12X.

INDICATIONS:

For temporary relief of various strains of influenza.

WARNINGS:

If pregnant or breast-feeding, ask a health care professional before use.

Keep out of reach of children. In case of overdose, get medical help or contact a Poison Control Center right away.

Do not use if tamper evident seal is broken or missing.

Store in cool, dry place.

KEEP OUT OF REACH OF CHILDREN:

In case of overdose, get medical help or contact a Poison Control Center right away.

DIRECTIONS:

10 drops orally, 3 times a day. Consult a physician for use in children under 12 years of age.

INDICATIONS:

For temporary relief of various strains of influenza.

INACTIVE INGREDIENTS:

Demineralized Water, 25% Ethanol

QUESTIONS:

Distributed by:
BioActive Nutritional, Inc.
1803 N. Wickham Rd.
Melbourne, FL 32935
bioactivenutritional.com

PACKAGE LABEL DISPLAY:

BIOActive Nutritional

RESPITORY TONIC F

HOMEOPATHIC

2 FL OZ (60 ml)